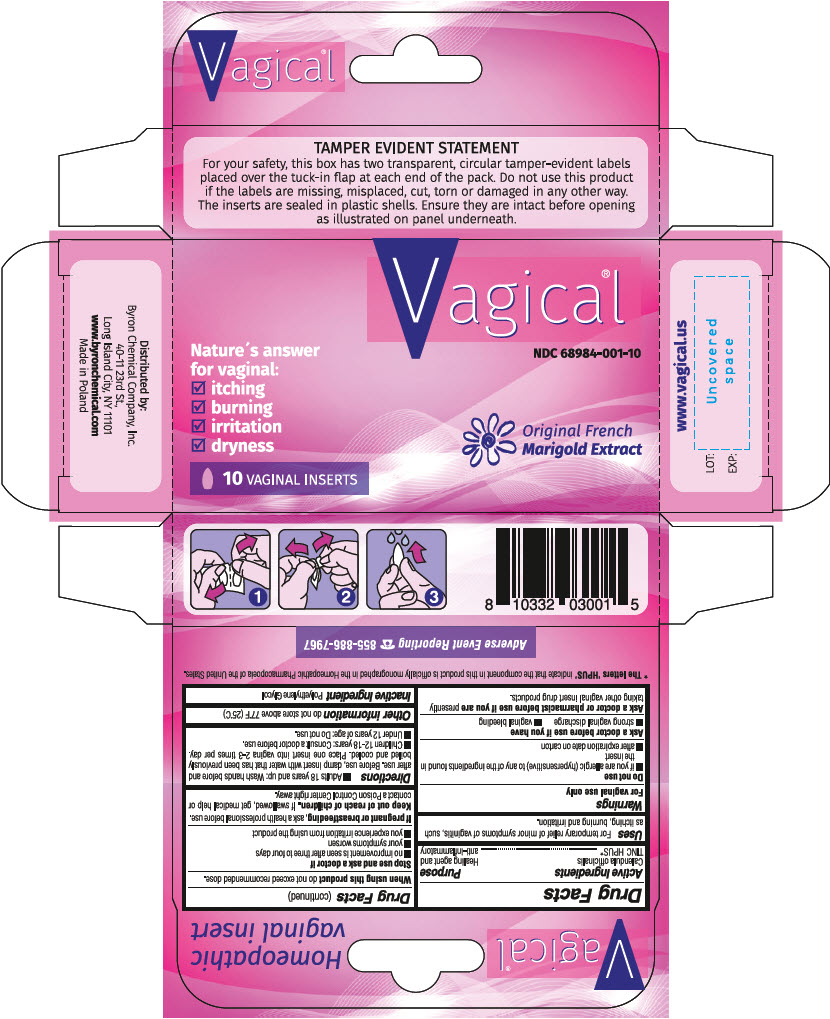 DRUG LABEL: Vagical
NDC: 68984-001 | Form: INSERT
Manufacturer: Farmina sp. z o.o.
Category: homeopathic | Type: HUMAN OTC DRUG LABEL
Date: 20250130

ACTIVE INGREDIENTS: CALENDULA OFFICINALIS FLOWERING TOP 150 mg/1 1
INACTIVE INGREDIENTS: POLYETHYLENE GLYCOL, UNSPECIFIED

Vagical

Active ingredient

Calendula officinalis TINC HPUS*

*The letters 'HPUS' indicate that the component in this product is officially monographed in the Homeopathic Pharmacopoeia of the United States.

Purpose

Healing agent and anti-inflammatory

Uses

For temporary relief of minor symptoms of vaginitis, such as itching, burning and irritation.

Warnings

For vaginal use only

Do not use

- if you are allergic (hypersensitive) to any of the ingredients found in the insert
- after expiration date on carton

Ask a doctor before use if you have

- strong vaginal discharge
- vaginal bleeding

Ask a doctor or pharmacist before use if you arepresently taking other vaginal insert drug products

When using this productdo not exceed recommended dose.

Stop use and ask a doctor if

- no improvement is seen after three to four days
- your symptoms worsen
- you experience irritation from using the product

PREGNANCY OR BREAST FEEDING

If pregnant or breastfeeding,ask a health professional before use.

Keep out of the reach of children.

If swallowed, get medical help or contact a Poison Control Center right away.

Directions

- Adults 18 years and up: Wash hands before and after use. Before use, damp insert with water that has been previously boiled and cooled. Place one insert into vagina 2-3 times per day.
- Children 12-18 years: Consult a doctor before use.
- Under 12 years of age: Do not use

Other information

do not store above 77 degrees F (25 degrees C)

Inactive ingredient

Polyethylene Glycol.

PRINCIPAL DISPLAY PANEL - 10 Insert Box

Vagical®

NDC 68984-001-10

Nature's answer
for vaginal:

- itching
- burning
- irritation
- dryness

Original French
Marigold Extract

10 VAGINAL INSERTS